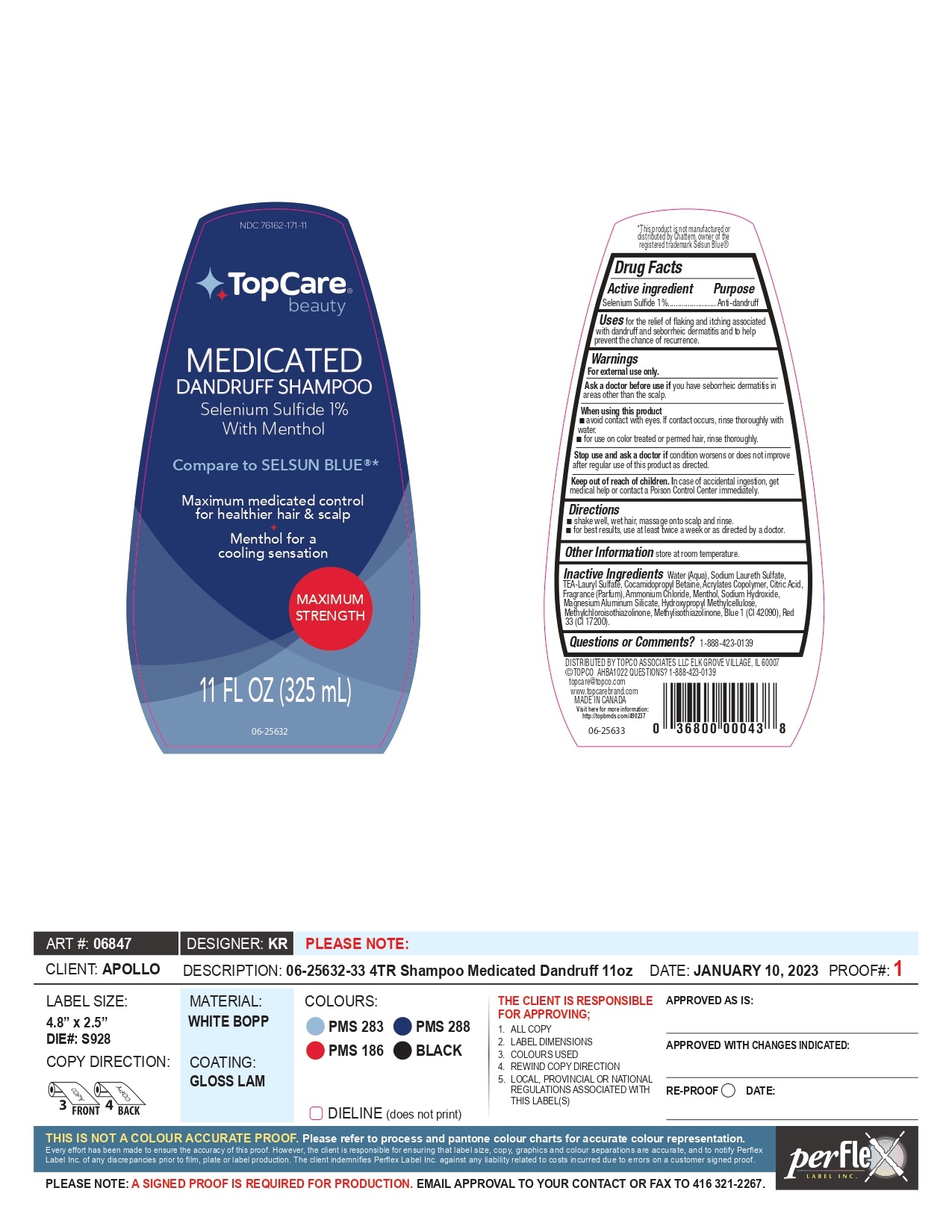 DRUG LABEL: Topco Associates
NDC: 76162-171 | Form: SHAMPOO
Manufacturer: Topco Associates
Category: otc | Type: HUMAN OTC DRUG LABEL
Date: 20250207

ACTIVE INGREDIENTS: SELENIUM SULFIDE 10 mg/1 mL
INACTIVE INGREDIENTS: SODIUM LAURETH SULFATE; AMMONIUM CHLORIDE; WATER; TRIETHANOLAMINE LAURYL SULFATE; COCAMIDOPROPYL BETAINE; MAGNESIUM ALUMINUM SILICATE; CITRIC ACID MONOHYDRATE; FRAGRANCE CLEAN ORC0600327; MAGNESIUM ALUMINUM SILICATE TYPE IA; HYPROMELLOSE, UNSPECIFIED; METHYLISOTHIAZOLINONE; FD&C BLUE NO. 1; METHACRYLIC ACID - ETHYL ACRYLATE COPOLYMER (4500 MPA.S); METHYLCHLOROISOTHIAZOLINONE; MENTHOL; SODIUM HYDROXIDE; D&C RED NO. 33

Topcare Medicated Shampoo-76162-171-11

ACTIVE INGREDIENT

Selenium Sulfide 1%

PURPOSE

anti dandruff

WARNINGS

For external use only.

Ask a doctor before useif you have seborrheic dermatitis in areas other than the scalp.

WHEN USING

■ avoid contact with eyes. If contact occurs, rinse thoroughly with water.
■ for use on color treated or permed hair, rinse thoroughly.

Stop use and ask a doctor ifcondition worsens or does not improve after regular use of this product as directed.

Keep out of reach of children.In case of accidental ingestion, get medical help or contact a Poison Control Center immediately.

DOSAGE AND ADMINISTRATION

■ shake well, wet hair, massage onto scalp and rinse.
■ for best results, use at least twice a week or as directed by a doctor.

STORAGE AND HANDLING

store at room temperature.

INACTIVE INGREDIENT

Water (Aqua), Sodium Laureth Sulfate, TEA-Lauryl Sulfate, Cocamidopropyl Betaine, Acrylates Copolymer, Citric Acid,
Fragrance (Parfum), Ammonium Chloride, Menthol, Sodium Hydroxide, Magnesium Aluminum Silicate, Hydroxypropyl Methylcellulose,
Methylchloroisothiazolinone, Methylisothiazolinone, Blue 1 (CI 42090), Red 33 (CI 17200).

QUESTIONS

1-888-423-0139

INDICATIONS AND USAGE

for the relief of flaking and itching associated with dandruff and seborrheic dermatitis and to help prevent the chance of recurrence.